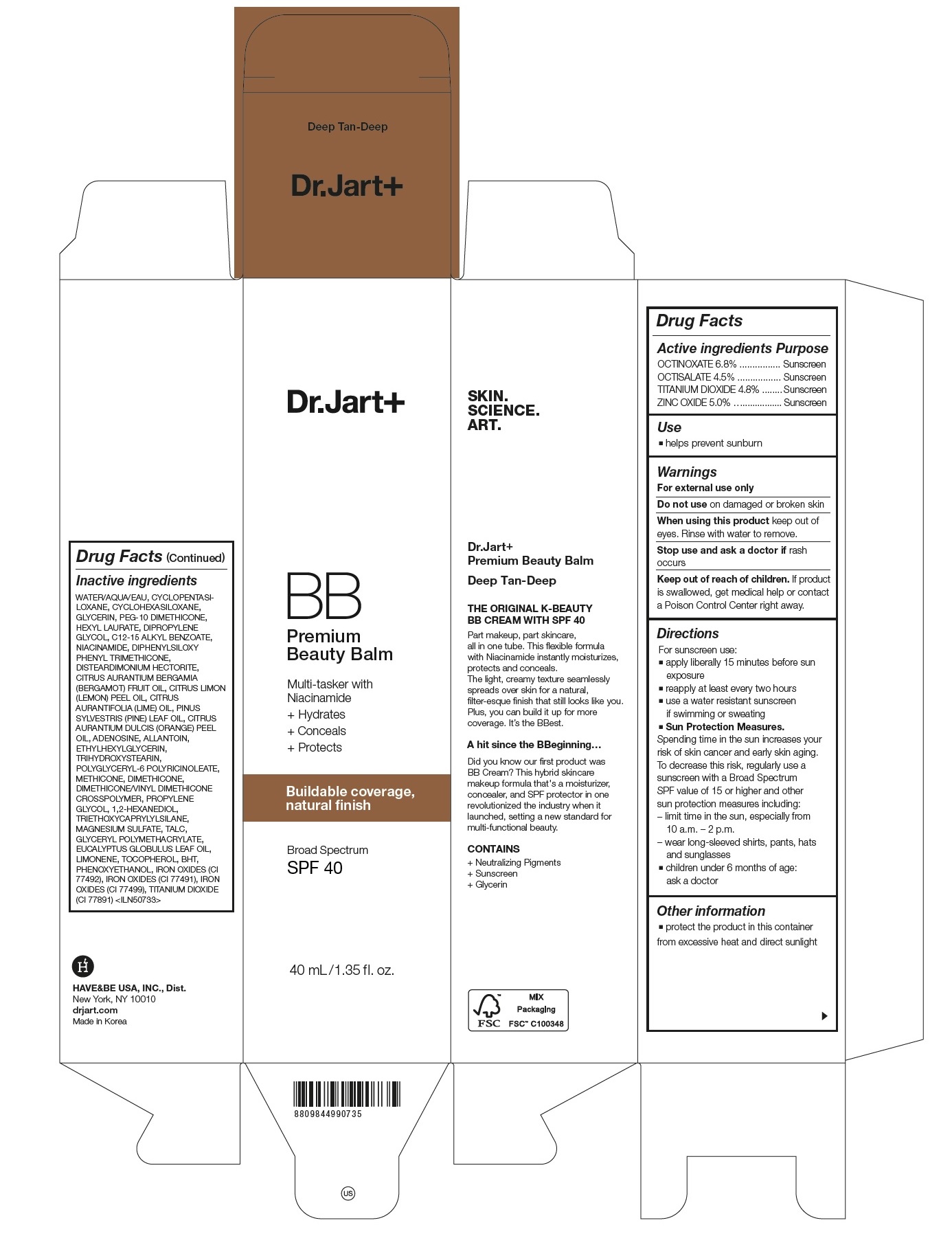 DRUG LABEL: Dr.Jart Premium Beauty Balm Deep Tan-Deep
NDC: 49404-151 | Form: CREAM
Manufacturer: Have & Be Co., Ltd.
Category: otc | Type: HUMAN OTC DRUG LABEL
Date: 20240620

ACTIVE INGREDIENTS: TITANIUM DIOXIDE 4.8 g/100 mL; ZINC OXIDE 5 g/100 mL; OCTINOXATE 6.8 g/100 mL; OCTISALATE 4.5 g/100 mL
INACTIVE INGREDIENTS: WATER; CYCLOMETHICONE 5; CYCLOMETHICONE 6; GLYCERIN; PEG-10 DIMETHICONE (600 CST); TALC; ALKYL (C12-15) BENZOATE; HEXYL LAURATE; DIPHENYLSILOXY PHENYL TRIMETHICONE; NIACINAMIDE; DIPROPYLENE GLYCOL; DISTEARDIMONIUM HECTORITE; MAGNESIUM SULFATE, UNSPECIFIED FORM; DIMETHICONE/VINYL DIMETHICONE CROSSPOLYMER (HARD PARTICLE); DIMETHICONE; FERRIC OXIDE YELLOW; TRIETHOXYCAPRYLYLSILANE; PHENOXYETHANOL; FERRIC OXIDE RED; METHICONE (20 CST); FERROSOFERRIC OXIDE; POLYGLYCERYL-6 POLYRICINOLEATE; TRIHYDROXYSTEARIN; ETHYLHEXYLGLYCERIN; ADENOSINE; ORANGE OIL, COLD PRESSED; LIME OIL, COLD PRESSED; PINE NEEDLE OIL (PINUS SYLVESTRIS); BUTYLATED HYDROXYTOLUENE; EUCALYPTUS OIL; BERGAMOT OIL; LEMON OIL, COLD PRESSED; TOCOPHEROL; ALLANTOIN; 1,2-HEXANEDIOL; PROPYLENE GLYCOL; POLYSORBATE 80; PLATINUM; PALMITOYL TRIPEPTIDE-1

49404-151 Dr.Jart+ Premium Beauty Balm Deep Tan-Deep

ACTIVE INGREDIENT

OCTINOXATE 6.8%
OCTISALATE 4.5%
TITANIUM DIOXIDE 4.8%
ZINC OXIDE 5.0%

PURPOSE

Sunscreen

INDICATIONS AND USAGE

Helps prevent sunburn

DOSAGE AND ADMINISTRATION

For sunscreen use:
■ apply liberally 15 minutes before sun exposure
■ reapply at least every two hours
■ use a water resistant sunscreen if swimming or sweating
■ Sun Protection Measures.
Spending time in the sun increases your risk of skin cancer and early skin aging. To decrease this risk, regularly use a sunscreen with a Broad Spectrum SPF value of 15 or higher and other sun protection measures including:
– limit time in the sun, especially from 10 a.m. – 2 p.m.
– wear long-sleeved shirts, pants, hats and sunglasses
■ children under 6 months of age: ask a doctor

WARNINGS

For external use only.
Do not use on damaged or broken skin.
When using this product, keep out of eyes. Rinse with water to remove.
Stop using and ask a doctor if rash occurs.

KEEP OUT OF REACH OF CHILDREN

Keep out of reach of the children. If product is swallowed, get medical help or contact a poison control center right away.

INACTIVE INGREDIENT

WATER, CYCLOPENTASILOXANE, CYCLOHEXASILOXANE, GLYCERIN, IRON OXIDES(CI 77492), PEG-10 DIMETHICONE, C12-15 ALKYL BENZOATE, HEXYL LAURATE, DIPHENYLSILOXY PHENYL TRIMETHICONE, NIACINAMIDE, DIPROPYLENE GLYCOL, IRON OXIDES(CI 77491), DISTEARDIMONIUM HECTORITE, MAGNESIUM SULFATE, IRON OXIDES(CI 77499), DIMETHICONE/VINYL DIMETHICONE CROSSPOLYMER, TALC, TITANIUM DIOXIDE (CI 77891), TRIETHOXYCAPRYLYLSILANE, DIMETHICONE, PHENOXYETHANOL, METHICONE, POLYGLYCERYL-6 POLYRICINOLEATE, TRIHYDROXYSTEARIN, ETHYLHEXYLGLYCERIN, CITRUS AURANTIUM DULCIS (ORANGE) PEEL OIL, ADENOSINE, CITRUS AURANTIFOLIA (LIME) OIL, PINUS SYLVESTRIS LEAF OIL, BHT, EUCALYPTUS GLOBULUS LEAF OIL, CITRUS LIMON (LEMON) PEEL OIL, CITRUS AURANTIUM BERGAMIA (BERGAMOT) FRUIT OIL, TOCOPHEROL, ALLANTOIN, GLYCERYL POLYMETHACRYLATE, PROPYLENE GLYCOL, 1,2-HEXANEDIOL, POLYSORBATE 80, PLATINUM POWDER, PALMITOYL TRIPEPTIDE-1

OTHER SAFETY INFORMATION

Protect the product in this container from excessive heat and direct sunlight